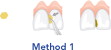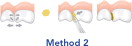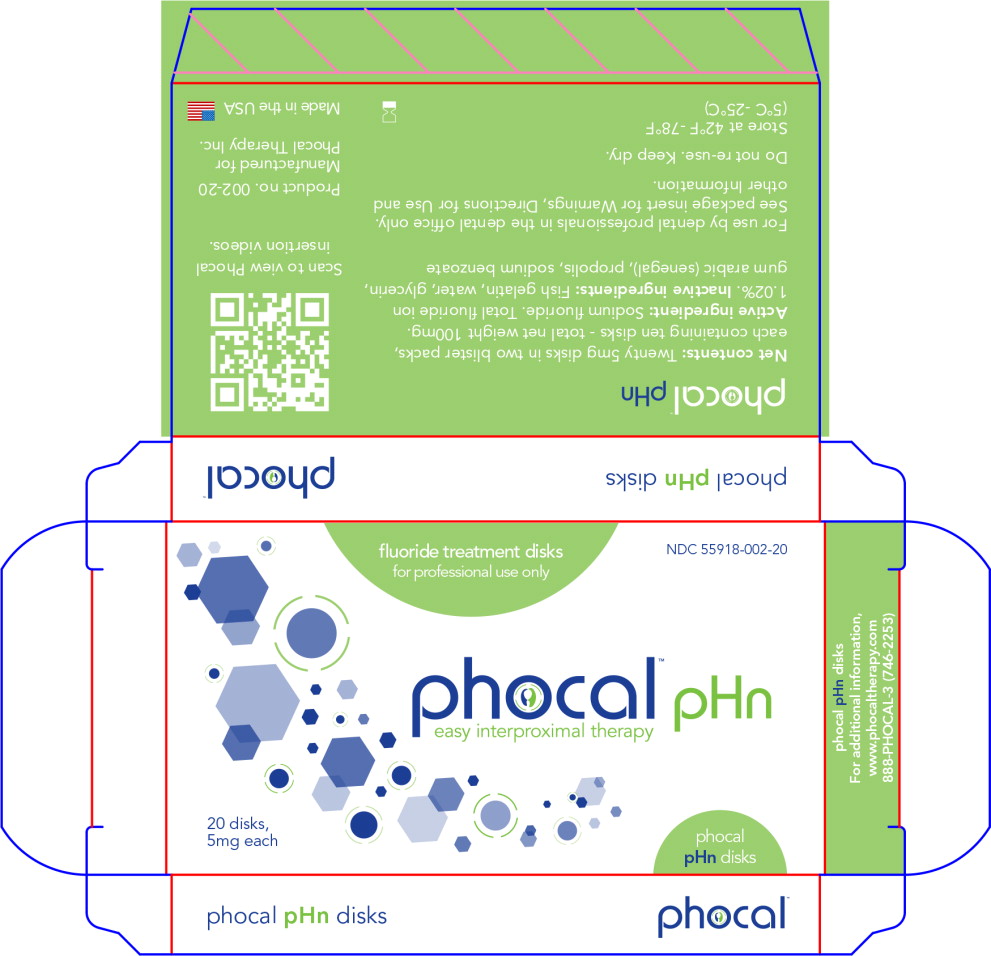 DRUG LABEL: Phocal pHn
NDC: 55918-002 | Form: DISC
Manufacturer: Phocal Therapy Inc
Category: prescription | Type: HUMAN PRESCRIPTION DRUG LABEL
Date: 20160823

ACTIVE INGREDIENTS: Sodium Fluoride 0.055 mg/1 1
INACTIVE INGREDIENTS: ACACIA; gelatin; PROPOLIS WAX; sodium benzoate; water

phocal™

easy interproximal therapy

INSTRUCTIONS FOR USE

Purpose and Indications

- Phocal disks are topical delivery vehicles designed to fluoridate interproximal tooth surfaces. This action aids in the prevention of dental caries on intact surfaces, arrests progress on surfaces with incipient carious lesions and enhances remineralization. Phocal disks are also effective at tooth restoration margins and furcations.
- Phocal disks are to be applied only by dental professionals at selected sites to achieve the desired benefits.

Description

- The patented Phocal topical fluoride disks are provided in two forms:
  - pink acidulated phosphate fluoride Apf disks
  - yellow non-acidic sodium fluoride pHn disks
- These thin, round disks contain 1.02% fluoride ions. Once positioned interproximally they rapidly expand, soften into a gel and release fluoride for approximately 10 minutes before biodegrading. This release period can be increased as explained in the Directions for Use.
- Each Phocal Apf disk contains 0.1135mg of sodium fluoride in a matrix of FD&C red 3, gum arabic, gelatin (of marine origin), propolis wax, phosphoric acid, sodium benzoate and water. These disks induce an optimized low pH environment that cleans and etches tooth surfaces and facilitates fluoride penetration and stimulates remineralization.
- Each Phocal pHn disk contains 0.1135mg of sodium fluoride in a matrix of gum arabic, gelatin (of marine origin), propolis wax, sodium benzoate and water. These disks are less acidic than the Phocal Apf disks and will not etch ceramic crowns or tooth-colored restorations while inducing fluoridation and remineralization.

Directions for Use

- There are different methods for the placement of Phocal fluoride disks.
- The choice of placement method and Phocal type is subject to the discretion of the dental professional and is usually dependent upon the nature of the site being treated, interproximal tightness and the strength and type of adjacent restorations and teeth.
- Prior to treatment using either of the placement methods below, all debris and calculus should be removed from the selected site(s) and the site(s) should remain dry during placement. Premature wetting softens the disks and can compromise correct interproximal placement.

Method 1 – Insertion of flat Phocal disks; recommended for anterior teeth and where spacing allows.

- When spacing allows, insert the flat Phocal disk interproximally with forceps and/or by hand directly between the contact points of the two adjacent teeth.

Method 2 – Insertion of flat Phocal disks with separation; recommended for posterior teeth and where spacing is restrictive.

- In some cases, separation with wedges or rings may be necessary prior to insertion.
- After separating the teeth by your chosen method of separation, insert the flat Phocal disk interproximally with forceps and/or by hand directly between the contact points of the two adjacent teeth.

- In rare cases nickel titanium springs, elastic O-rings or Maxian strips can be used to separate teeth but this is usually a slower process which requires two visits: one for separation and then one for disk placement.
- To accelerate the initial reactions of Phocal disks a curing light can be applied for 3-10 seconds.
- To extend the fluoride release time period, a varnish can be applied to partially cover the interproximal site or disk occlusally, buccally or/and lingually. However the disk should not be completely coated with varnish.
- To shorten the release time the disks can be removed using an appropriate instrument, dental floss and/or aspiration.
- If Phocal Apf is used, in order to guard against possible etching of porcelain crowns or tooth-colored restorations, a protective matrix should be used. With Phocal pHn there is no risk of etching.
- Advise the patient not to eat, drink or rinse for at least 30 minutes after treatment.
- If multiple applications are necessary, treat no more than 8 sites at a time and delay subsequent Phocal applications for at least a day.
- If deemed necessary, patients may be recalled at intervals of 2 to 12 months for repeated treatments.
- Phocal disks are versatile, and with specific gentle moisturization they can be trimmed, rolled, or folded to fit other inaccessible areas such as furcations.

Warnings

- In rare cases, sensitivity or adverse reactions may be experienced. In such cases immediately remove the disks while preventing swallowing and refer the patient to a physician.
- Patients less than 12 years old and patients with special needs should remain under professional supervision until the Phocal disks have biodegraded or have been removed.
- The disks are not intended for systemic ingestion and should be kept out of children's reach. If more than 20 disks are accidently swallowed, seek immediate medical assistance.
- Phocal should not be applied in sites with: gingival inflammation, immediately prior to or after oral soft tissue surgery and in cases of known allergies to any of the Phocal ingredients.
- Phocal is to be sold as unbroken boxes with all disks sealed within the blister packs and is to be used for application in the dental office by professionals only.
- When Phocal treatment is utilized, routine systemic and topical administrations of fluoride should be suspended during the day of application.
- Recommended storage temperatures are 40°F-78°F (5°C-25°C).

Responsibility of the Professional

- Phocal disks have been developed for use only by licensed professionals in the dental care setting. Phocal Therapy, Inc. warrants the quality of the products for the uses described and when used in the manners outlined here and in our sales and delivery documents. It is the responsibility of the professional to use the products.

For additional information
www.phocaltherapy.com
888-Phocal-3 (746-2253)

Principal Display panel – Box Label

NDC 55918-002-20

fluoride treatment disks
for professional use only

phocal™ pHn

easy interproximal therapy

20 disks,
5mg each

phocal

pHn disks